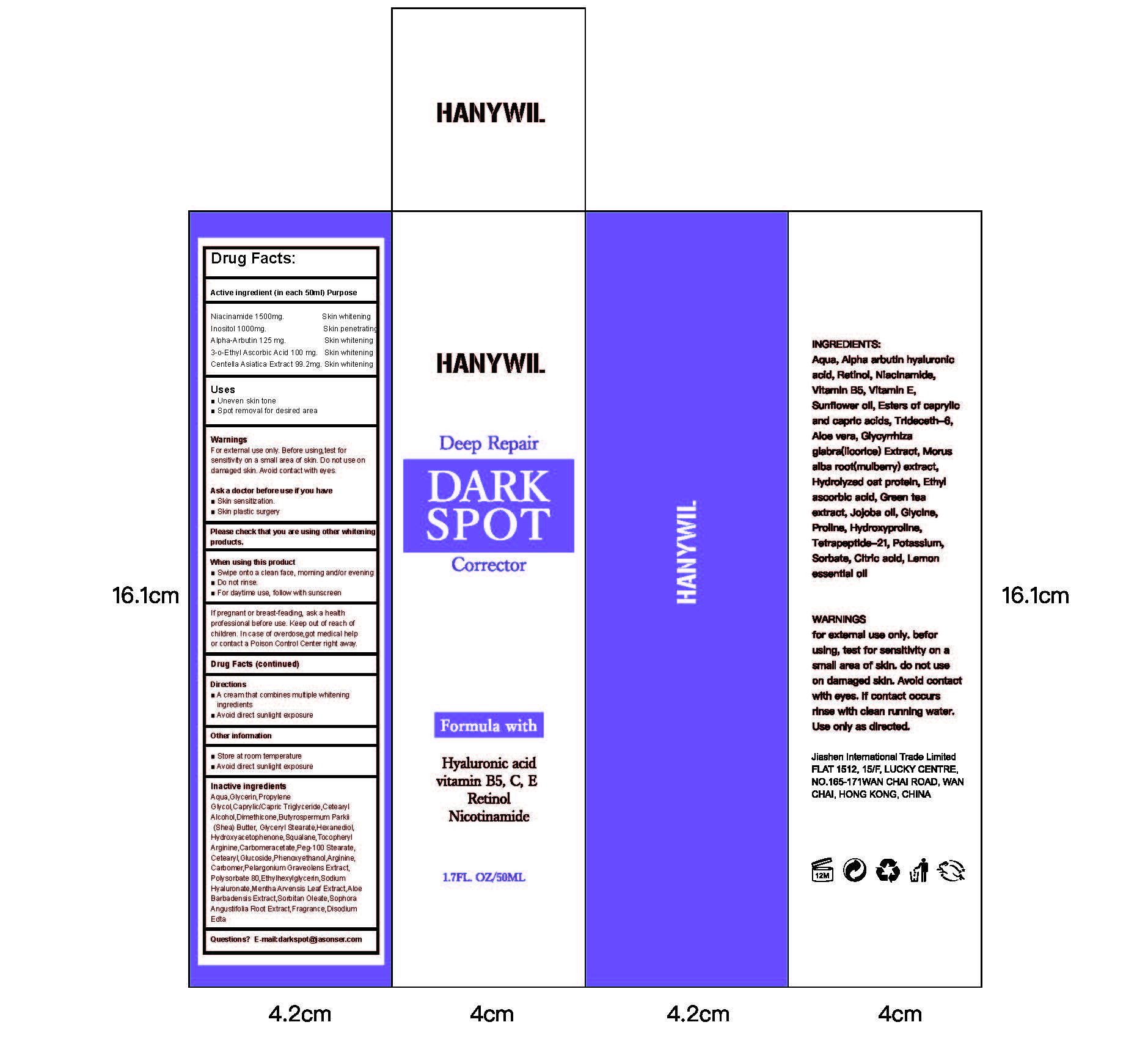 DRUG LABEL: Deep Repair DARK SPOT
NDC: 84867-001 | Form: CREAM
Manufacturer: Deep Repair DARK SPOT
Category: otc | Type: HUMAN OTC DRUG LABEL
Date: 20241102

ACTIVE INGREDIENTS: INOSITOL 1000 mg/50 mL; 3-O-ETHYL ASCORBIC ACID 100 mg/50 mL; ALPHA-ARBUTIN 125 mg/50 mL; NIACINAMIDE 1500 mg/50 mL; CENTELLA ASIATICA 99.2 mg/50 mL
INACTIVE INGREDIENTS: VITAMIN E POLYETHYLENE GLYCOL SUCCINATE; HYDROXYPROLINE; CITRIC ACID; ALOE VERA LEAF EXTRACT; MORUS ALBA ROOT; JOJOBA OIL; PROLINE; DS-677 POTASSIUM; CAPRYLIC/CAPRIC/LAURIC TRIGLYCERIDE; SORBATE ION; HYDROLYZED CORN PROTEIN (ENZYMATIC; 1500 MW); TETRAPEPTIDE-21; TRIDECETH-6; GLYCYRRHIZA GLABRA (LICORICE) ROOT EXTRACT; GREEN TEA LEAF; GLYCINE; AQUA; SUNFLOWER OIL; CITRUS LIMON (LEMON) FRUIT EXTRACT

Active ingredient (in each 50ml) Purpose
Niacinamide 1500mg.
Inositol 1000mg.
Alpha-Arbutin 125 mg.
3-0-Ethyl Ascorbic Acid 100 mg
Centella Asiatica Extract 99.2mg

PURPOSE

Deep Repair DARKSPOT
Corrector

INACTIVE INGREDIENT

Aqua,Glycerin,Propylene
Glycol,Caprylic/Capric Triglyceride,Cetearyl
Alcohol,Dimethicone,Butyrospermum Parkii
(Shea) Butter, Glyceryl Stearate,Hexanediol,
Hydroxyacetophenone,Squalane,Tocopheryl
Arginine,Carbomeracetate,Peg-100 Stearate,
Cetearyl,Glucoside,Phenoxyethanol,Arginine,
Carbomer,Pelargonium Graveolens Extract,
Polysorbate 80,Ethylhexylglycerin,Sodium
Hyaluronate,Mentha Arvensis Leaf Extract,Aloe
Barbadensis Extract,Sorbitan Oleate,Sophora
Angustifolia Root Extract,Fragrance,Disodium
Edta

WARNINGS

If pregnant or breast-feading, ask a health
professional before use. Keep out of reach of
children. In case of overdose,got medical help
or contact a Poison Control Center right away.

STOP USE

If pregnant or breast-feading, ask a health
professional before use. Keep out of reach of
children. In case of overdose,got medical help
or contact a Poison Control Center right away.

DO NOT USE

If pregnant or breast-feading, ask a health
professional before use. Keep out of reach of
children. In case of overdose,got medical help
or contact a Poison Control Center right away.

Keep out of reach of children. In case of overdose,got medical help
or contact a Poison Control Center right away.

WHEN USING

When using this productSwipe onto a clean face, morning and/or evening
mDo not rinse.
For daytime use, follow with sunscreen

Uses
Uneven skin tone
Spot removal for desired area

DOSAGE AND ADMINISTRATION

take appropriate cream to the dark area